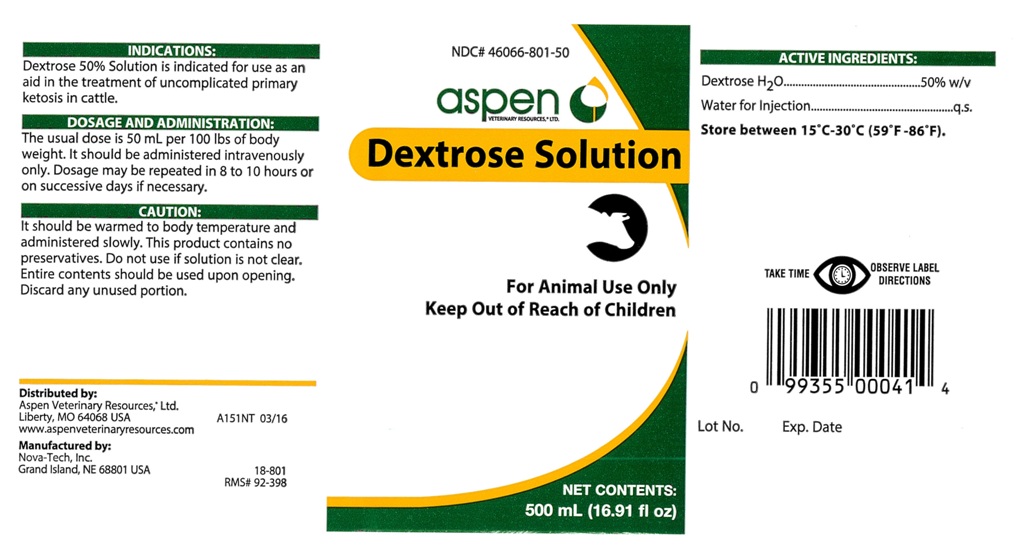 DRUG LABEL: Dextrose Solution
NDC: 46066-801 | Form: INJECTION, SOLUTION
Manufacturer: Aspen Veterinary
Category: animal | Type: OTC ANIMAL DRUG LABEL
Date: 20160804

ACTIVE INGREDIENTS: Dextrose Monohydrate 250 g/500 mL

Dextrose Solution

INDICATIONS:

Dextrose 50% Solution is indicated for use as an
aid in the treatment of uncomplicated primary
ketosis in cattle.

DOSAGE AND ADMINISTRATION:

The usual dose is 50 mL per 100 lbs of body
weight. It should be administered intravenously
only. Dosage may be repeated in 8 to 10 hours or
on successive days if necessary.

CAUTION:

It should be warmed to body temperature and
administered slowly. This product contains no
preservatives. Do not use if solution is not clear.
Entire contents should be used upon opening.
Discard any unused portion.

GENERAL PRECAUTIONS

For Animal Use Only

Keep Out of Reach of Children

INFORMATION FOR OWNERS/CAREGIVERS

NET CONTENTS:
500 mL (16.91 fl oz)

ACTIVE INGREDIENTS:

Dextrose H2O............................50% w/v
Water for Injection.............................q.s.

STORAGE AND HANDLING

Store between 15 degrees C - 30 degrees C (59 degrees F - 86 degrees F).

INFORMATION FOR OWNERS/CAREGIVERS

Distributed by:
Aspen Veterinary Resources®, Ltd.
Liberty, MO 64068 USA A151NT 03/16
www.aspenveterinaryresources.com

Manufactured by:
Nova-Tech, Inc.
Grand Island, NE 68801 USA 18-801
RMS# 92-398

Lot No. Exp. Date

GENERAL PRECAUTIONS

TAKE TIME OBSERVE LABEL DIRECTIONS